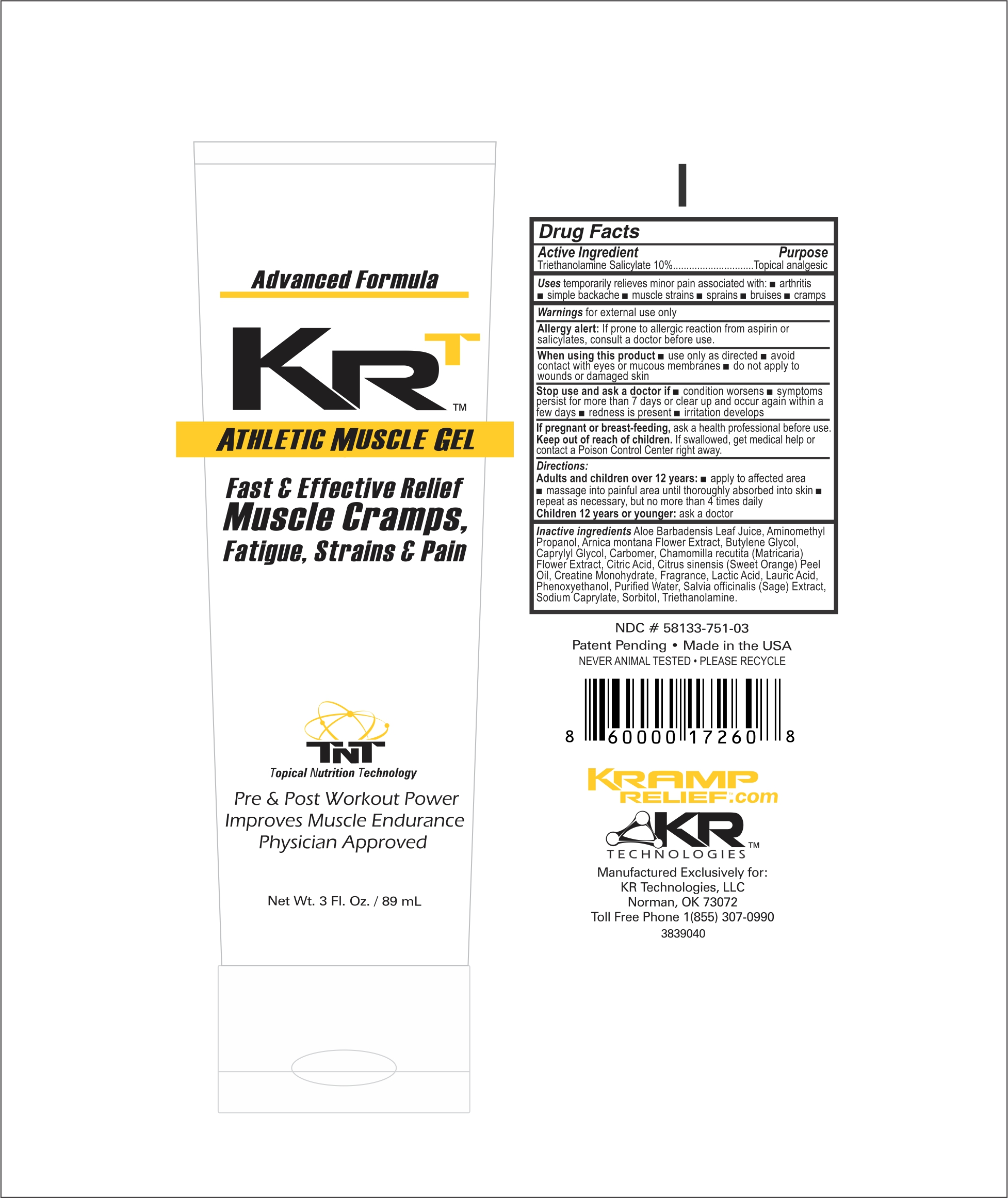 DRUG LABEL: KRT Athletic Muscle Gel
NDC: 58133-751 | Form: GEL
Manufacturer: Cosmetic Specialty Labs, Inc.
Category: otc | Type: HUMAN OTC DRUG LABEL
Date: 20210812

ACTIVE INGREDIENTS: TROLAMINE SALICYLATE 10 g/100 mL
INACTIVE INGREDIENTS: CARBOMER 940; ANHYDROUS CITRIC ACID; TROLAMINE; ORANGE OIL, DISTILLED; SAGE; SODIUM CAPRYLATE; BUTYLENE GLYCOL; CREATINE MONOHYDRATE; LACTIC ACID; CAPRYLYL GLYCOL; CHAMOMILE; ALOE VERA LEAF; LAURIC ACID; AMINOMETHYLPROPANOL; ARNICA MONTANA FLOWER; PHENOXYETHANOL; WATER; SORBITOL

Active Incredient

Triethanolamine Salicylate 10%

Purpose

Topical analgesic

Uses

temporarily relieves minor pain associated with • arthritis • simple backache • muscle strains • sprains • bruises • cramps

Warnings

for external use only

Allergy alert:

If prone to allergic reaction from aspirin or salicylates, consult a doctor before use.

When using this product • use only as directed • avoid contact with eyes or mucous membranes • do not apply to wounds or damaged skin

Stop use and ask a doctor if • condition worsens • symptoms persist for more than 7 days or clear up and occur again within a few days • redness is present • irritation develops

KEEP OUT OF REACH OF CHILDREN

If pregnant or breast-feeding, ask a health professional before use.

Keep out of reach of children. If swallowed, get medical help or contact a Poison Control Center right away.

Directions:

Adults and children over 12 years: • apply to affected area • massage into painful area until thoroughly absorbed into skin • repeat as necessary, but no more than 4 times daily

Children 12 years or younger: ask a doctor

Inactive Ingredients

Aloe Barbadensis Leaf Juice, Aminomethyl Propanol, Arnica montana Flower Extract, Butylene Glycol, Caprylyl Clycol, Carbomer, Chamomila recutita (Matricaria) Flower Extract, Citric Acid, Citrus sinensis (Sweet Orange) Peel Oil, Creatine Monohydrate, Fragrance, Lactic Acid, Lauric Acid, Phenoxyethanol, Purified Water, Salvia officinalis (Sage) Extract, Sodium Caprylate, Sorbitol, Triethanolamine.